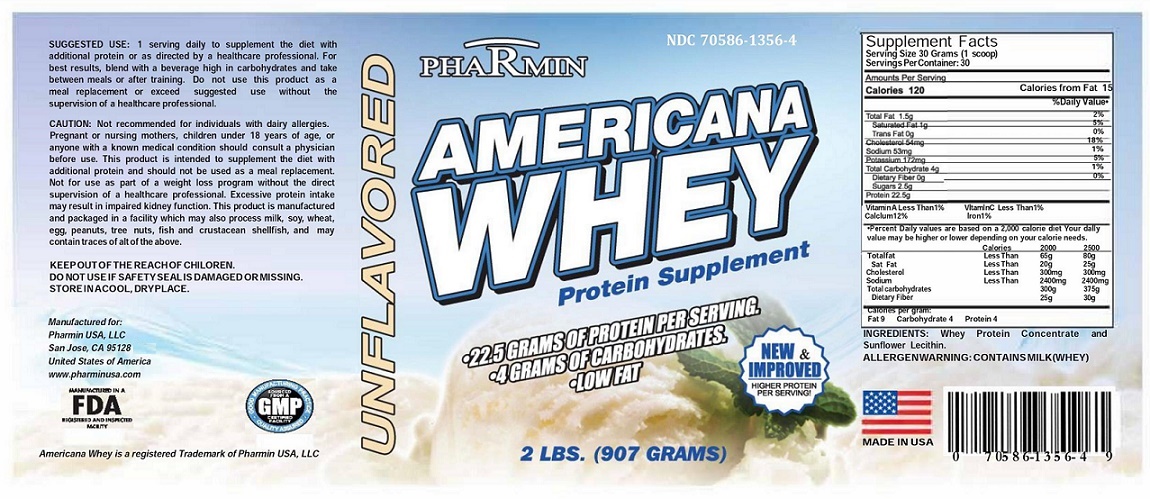 DRUG LABEL: AMERICANA WHEY Protein Supplement
NDC: 70586-1356 | Form: POWDER
Manufacturer: Pharmin USA, LLC
Category: other | Type: DIETARY SUPPLEMENT
Date: 20171228

ACTIVE INGREDIENTS: WHEY 80 g/100 g
INACTIVE INGREDIENTS: LECITHIN, SUNFLOWER

AMERICANA WHEY Protein Supplement

HIGHLIGHTS OF PRESCRIBING INFORMATION Protein Supplement

Americana Whey- protein supplement powder for ORAL use

Artificial Bovine Growth Hormone Free

Non-GMO

1. INDICATIONS AND USAGE:

Americana Whey is a source of essential branched-chain amino acids (BCASS) leucine, isoleucine, and valine. Americana Whey helps forming blood vessels, supporting immune systems and regulating metabolism. Americana Whey recovers muscle fatigue from post workout as well as it helps building and repairing muscles.

2. DOSAGE AND ADMINISTRATION

One serving daily to supplement the diet with additional protein or as directed by a healthcare professional. For best results, blend with a beverage high in carbohydrates and take between meals or after training. Do not use this product as a meal replacement or exceed suggested use without the supervision of a healthcare professional.

3. DOSAGE FORMS AND STRENGTHS

Dry Powder 22.5 mg protein per 30 grams (1 scoop)

4. CONTRA-INDICATIONS

History of hypersensitivity to any of the components in the formula.

5. WARNINGS AND PRECAUTIONS

rGBH growth is a genetically engineered artificial growth hormone injected into dairy cows to increase milk production. The growth hormones can lead to utter infections, which are treated with antibiotics. Both rBGH growth hormones and antibiotics can then be passed on to humans through the milk. Americana Whey is rGBH free product.

6. MECHANISM OF ACTION

Cells growth via carrying essential amino acids.

7. DRUG INTERACTIONS

Severe interactions were not reported. Nevertheless, to avoid interactions with other drugs, the patient shall inform the physician if she/he is taking another medicine.

8. ADVERSE REACTIONS

May cause stomach upset. If occurred take it after meals.

9. PRECAUTIONS

This product has been ordered for a particular condition, therefore, it should not be used for other conditions and not give to anyone else. Keep this and all medicines out of the reach of children. This product should not be used after expiration date.

10. PREGNANCY AND LACTATION

There is no available data to evaluate teratogenic or fetotoxic effects. Therefore, it should not be used during pregnancy and lactation.

11. OVERDOSAGE

Non-reported

12. EFFECTS ON ABILITY TO DRIVE

Non-reported

13. HOW SUPPLIED/STORAGE AND HANDLING

Americana Whey protein supplement, intended for oral administration, is white powder containing 22.5 grams per serving supplied as follows:

NDC 70586-1356-4 907 grams bottles

14. STORAGE:

Store at 20° to 25°C (68° to 77°F) [See USP Controlled Room Temperature].

15. INGREDIENTS

Whey protein concentrate and Sunflower Lecithin.

Package label principal display panel (2 LBS- 907 GRAMS)

NDC 70586-1356-4

AMERICAN WHEY protein supplement

- 22.5 grams of protein per serving
- 4 grams of carbohydrates
- Low fat
- Unflavored
- Solubility over a wide pH range
- Excellent emulsification properties
- Foam stability
- Gelation and water-binding properties
- Available with sunflower and no side effects such as upset stomach and bloating
- Clear with little cloudiness
- Low in fats and lactose
- Compatible with all juices, milk and easily dissolvable

Supplement Facts; Serving Size 30 Grams (1 scoop) Serving Per Container:30
Amount Per Serving
Calories 120 |  |  | Calories from Fat 15
 |  |  | % Daily Value*
Total Fat 1.5 g |  |  | 2 %
Saturated Fat 1 g |  |  | 5 %
Trans Fat 0g |  |  | 0 %
Cholesterol 54 mg |  |  | 18%
Sodium 53 mg |  |  | 1%
Potassium 172 mg |  |  | 5%
Total Carbohydrate 4 g |  |  | 1 %
Dietary Fiber 0g |  |  | 0 %
Sugars 2.5 g
Protein 22.5 g
Vitamin A less that 1% |  |  | VitaminC Less that 1%
Calcium 12 % |  |  | Iron 1%
*Percent Daily Values are based on a 2,000 Calories diet.; Your daily value may be higher or lower depending on your calorie needs.
 | Calories | 2000 | 2500
Total Fat | LessThan | 65g | 80g
Sat.Fat | LessThan | 20g | 25g
Cholesterol | LessThan | 300mg | 300mg
Sodium | LessThan | 2400mg | 2400mg
Total carbohydrates |  | 300g | 375g
Dietary Fiber |  | 25g | 30g
Calories per gram:
Fat 9 Carbohydrate 4 protein 4-Cyvex Nutrition dba Nutegrity

SUGGESTED USE:

1 serving daily to supplement the diet with additional protein or as directed by a healthcare professional. For best results, blend with a beverage high in carbohydrates and take between meals or after training. Do not use this product as a meal replacement or exceed suggested use without the supervision of a healthcare professional.

KEEP THIS AND ALL MEDICATIONS OUT OF REACH OF CHILDREN.

DO NOT USE IF SAFETY SEAL IS DAMAGED OR MISSING. STORE IN A COOL, DRY PLACE.

Americana Whey is manufactured in a FDA and GMP certified facility.

Manufactured For:

Pharmin USA, LLC
2375 Lindbergh Avenue
San Jose, California 95128
United States of America

www.pharminusa.com

*Americana Whey is a registered Trademark of Pharmin USA, LLC.

Made in USA